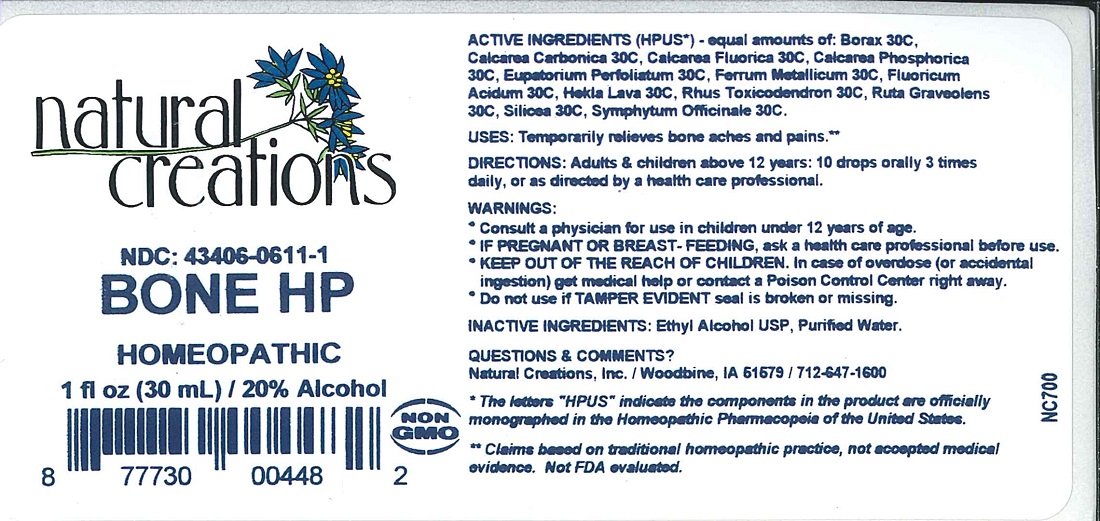 DRUG LABEL: BONE HP
NDC: 43406-0611 | Form: LIQUID
Manufacturer: Natural Creations, Inc.
Category: homeopathic | Type: HUMAN OTC DRUG LABEL
Date: 20251113

ACTIVE INGREDIENTS: SODIUM BORATE 30 [hp_C]/1 mL; OYSTER SHELL CALCIUM CARBONATE, CRUDE 30 [hp_C]/1 mL; CALCIUM FLUORIDE 30 [hp_C]/1 mL; TRIBASIC CALCIUM PHOSPHATE 30 [hp_C]/1 mL; EUPATORIUM PERFOLIATUM FLOWERING TOP 30 [hp_C]/1 mL; IRON 30 [hp_C]/1 mL; HYDROFLUORIC ACID 30 [hp_C]/1 mL; HEKLA LAVA 30 [hp_C]/1 mL; TOXICODENDRON PUBESCENS LEAF 30 [hp_C]/1 mL; RUTA GRAVEOLENS FLOWERING TOP 30 [hp_C]/1 mL; SILICON DIOXIDE 30 [hp_C]/1 mL; COMFREY ROOT 30 [hp_C]/1 mL
INACTIVE INGREDIENTS: WATER; ALCOHOL

BONE HP

ACTIVE INGREDIENT

ACTIVE INGREDIENTS (HPUS*) - equal amounts of: Borax Veneta 30C, Calcarea Carbonica 30C, Calcarea Fluorica 30C, Calcarea Phosphorica 30C, Eupatorium Perfoliatum 30C, Ferrum Metallicum 30C, Fluoricum Acidum 30C, Hekla Lava 30C, Rhus Toxicodendron 30C, Ruta Graveolens 30C, Silicea 30C, Symphytum Officinale 30C.

PURPOSE

USES: Temporarily relieves bone aches and pains.**

INDICATIONS AND USAGE

USES: Temporarily relieves bone aches and pains.**

DOSAGE AND ADMINISTRATION

DIRECTIONS: Adults & children above 12 years: 10 drops orally 3 times daily, or as directed by a health care professional.

WARNINGS:

* Consult a physician for use in children under 12 years of age.

* IF PREGNANT OR BREAST-FEEDING, ask a health care professional before use.

* KEEP OUT OF THE REACH OF CHILDREN. In case of overdose (or accidental ingestion) get medical help or contact a Poison Control Center

right away.

* Do not use if TAMPER EVIDENT seal is broken or missing.

KEEP OUT OF REACH OF CHILDREN

KEEP OUT OF THE REACH OF CHILDREN. In case of overdose (or accidental ingestion) get medical help or contact a Poison Control Center right away.

INACTIVE INGREDIENTS: Ethyl Alcohol USP, Purified Water.

QUESTIONS & COMMENTS?

Natural Creations, Inc. / Woodbine, IA 51579 / 712-647-1600

REFERENCES

* The letters "HPUS" indicate the components in the product are officially monographed in the Homeopathic Pharmacopeia of the United States.

** These statements have not been reviewed by the FDA. They are based on traditional homeopathic practice.

LOT:

PACKAGE LABEL

NDC: 43406-0611-1

BONE HP

HOMEOPATHIC

1 fl oz (30 mL) / 20% Alcohol

UPC: 877730004482 NON GMO LOGO